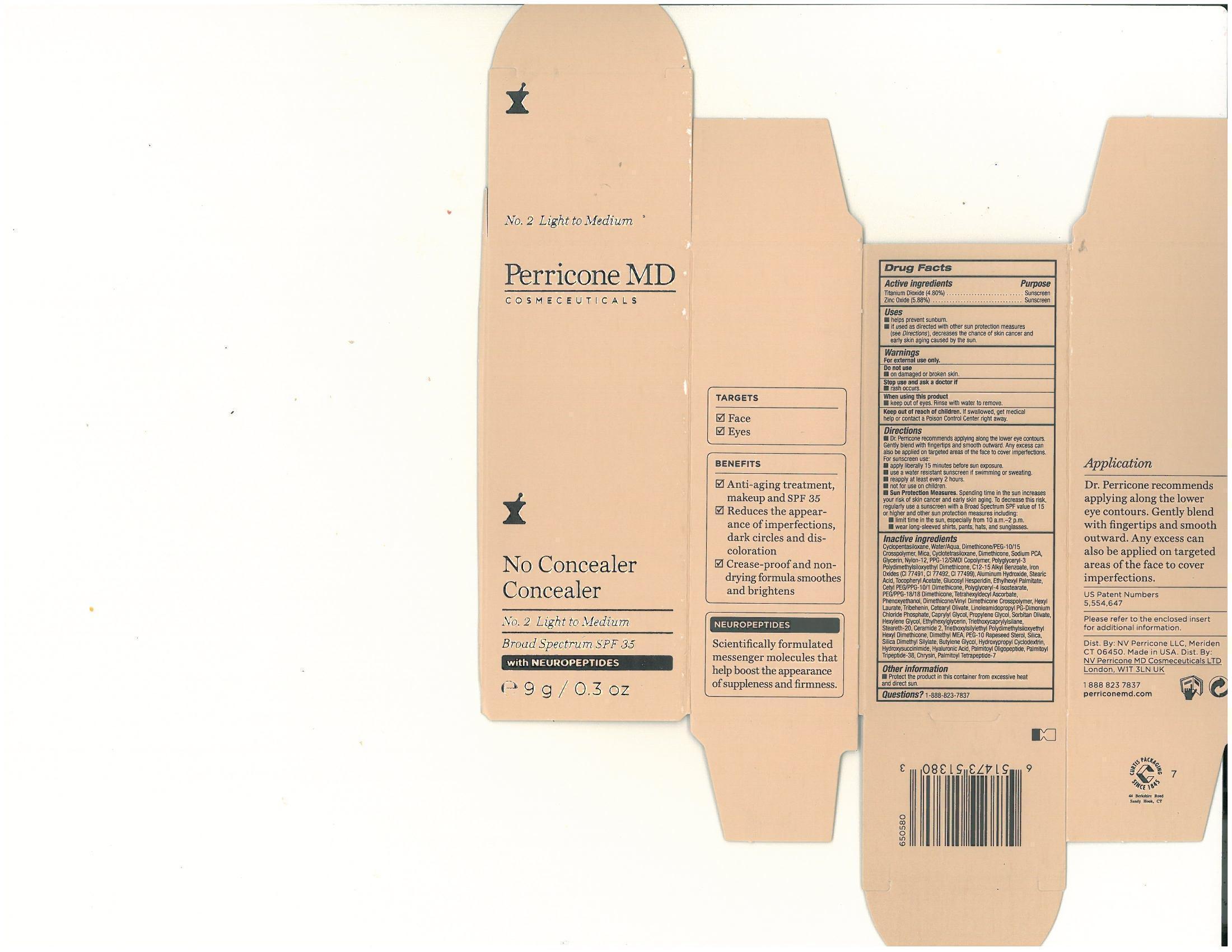 DRUG LABEL: No Concealer Concealer No.2 Light to Medium
NDC: 62742-4062 | Form: CREAM
Manufacturer: Allure Labs, Inc
Category: otc | Type: HUMAN OTC DRUG LABEL
Date: 20140411

ACTIVE INGREDIENTS: Titanium Dioxide 48 mg/1 g; Zinc Oxide 58.8 mg/1 g
INACTIVE INGREDIENTS: CYCLOMETHICONE 5; WATER; MICA; DIMETHICONE; SODIUM PYRROLIDONE CARBOXYLATE; GLYCERIN; NYLON-12 ; PPG-12/SMDI COPOLYMER; C12-15 Alkyl Benzoate; FERRIC OXIDE RED ; FERRIC OXIDE YELLOW; FERROSOFERRIC OXIDE; STEARIC ACID ; .ALPHA.-TOCOPHEROL ACETATE ; ETHYLHEXYL PALMITATE; POLYGLYCERYL-4 ISOSTEARATE ; PEG/PPG-18/18 DIMETHICONE ; DIMETHICONE/VINYL DIMETHICONE CROSSPOLYMER (SOFT PARTICLE) ; TETRAHEXYLDECYL ASCORBATE ; PHENOXYETHANOL ; HEXYL LAURATE ; TRIBEHENIN  ; CETEARYL OLIVATE ; LINOLEAMIDOPROPYL PG-DIMONIUM CHLORIDE PHOSPHATE ; CAPRYLYL GLYCOL; PROPYLENE GLYCOL ; SORBITAN OLIVATE ; HEXYLENE GLYCOL; ETHYLHEXYLGLYCERIN; TRIETHOXYCAPRYLYLSILANE; STEARETH-20; CERAMIDE 2; DEANOL; PEG-10 RAPESEED STEROL; SILICON DIOXIDE; SILICA DIMETHYL SILYLATE; BUTYLENE GLYCOL; HYDROXYPROPYL .BETA.-CYCLODEXTRIN; N-HYDROXYSUCCINIMIDE; HYALURONIC ACID; PALMITOYL OLIGOPEPTIDE ; PALMITOYL LYSYLDIOXYMETHIONYLLYSINE; CHRYSIN; PALMITOYL TETRAPEPTIDE-7 ; CYCLOMETHICONE 4; ALUMINUM HYDROXIDE

Drug Facts

Active Ingredients:

Titanium Dioxide 4.8%

Zinc Oxide 5.88%

PURPOSE:

Sunscreen

Uses:

- Helps prevent sunburn
- If used as directed with other sun protection measures (see Directions) decreases the chance of skin cancer and early skin aging caused by sun.

Warning:

- For External Use Only

- Do not use on damaged or broken skin

WHEN USING THIS PRODUCT:

- keep out of eyes. Rinse with water to remove

STOP USE AND ASK DOCTOR IF

rash occurs.

KEEP OUT OF REACH OF CHILDREN

- if swallowed get medical help or contact a poison control center right away

DIRECTIONS:

Dr. Perricone recommends applying along the lower eye contours. Gently Blend with fingertips and smooth outward. Any excess can also be applied on targeted areas of the face to cover imperfections.

STORAGE AND HANDLING

Protect the product in this container from excessive heat and direct sun

INACTIVE INGREDIENT

Cyclopentasiloxane, Water/Aqua, Dimethicone/PEG-10/15 Crosspolymer, Mica, Cyclotetrasiloxane, Dimethicone, Sodium PCA, Glycerin, Nylon-12, PPG-12 SMDI Copolymer, Polyglyceryl-3 Polydimethylsiloxyethyl Dimethicone,C12-15 Alkyl Benzoate, Iron Oxides (CI77491, CI 77492, CI 77499), Aluminum Hydroxide, Stearic Acid, Tocopheryl Acetate, Glucosyl Hesperidin, Ethylhexyl Palmitate, Cetyl PEG/PPG-10/1 Dimethicone, Polyglyceryl-4 Isostearate, PEG/PPG-18/18 Dimethicone, Tetrahexyldecyl Ascorbate, Phenoxyethanol, Dimethicone/Vinyl Dimethicone Crosspolymer, Hexyl Laurate, Tribehenin, Cetearyl Olivate, Linoleamidopropyl PG-Dimonium Chloride Phosphate, Caprylyl Glycol, Propylene Glycol, Sorbitan Olivate, Hexylene Glycol, Ethylhexylglycerin, Triethoxycaprylylsilane, Steareth-20, Ceramide 2, Triethoxysilylethyl Polydimethylsiloxyethyl Hexyl Dimethicone, Dimethyl MEA, PEG-10 Rapeseed Sterol, Silica, Silica DimethylSilylate, Butylene Glycol, Hydroxypropyl Cyclodextrin, Hydoxysuccinimide, Hyaluronic Acid, Palmitoyl Oligopeptide, Palmitoyl Tripeptide-38, Chrysin, Plamitoyl tetrapeptide-7

PACKAGE LABEL

Distributed By (US): NV Perricone LLC Meriden CT 06450 Made in USA

Distributed By (UK): NV Perricone MD Cosmeceuticals Ltd London W1T 3LN UK

www.perriocnemd.com 1-888-823-7837